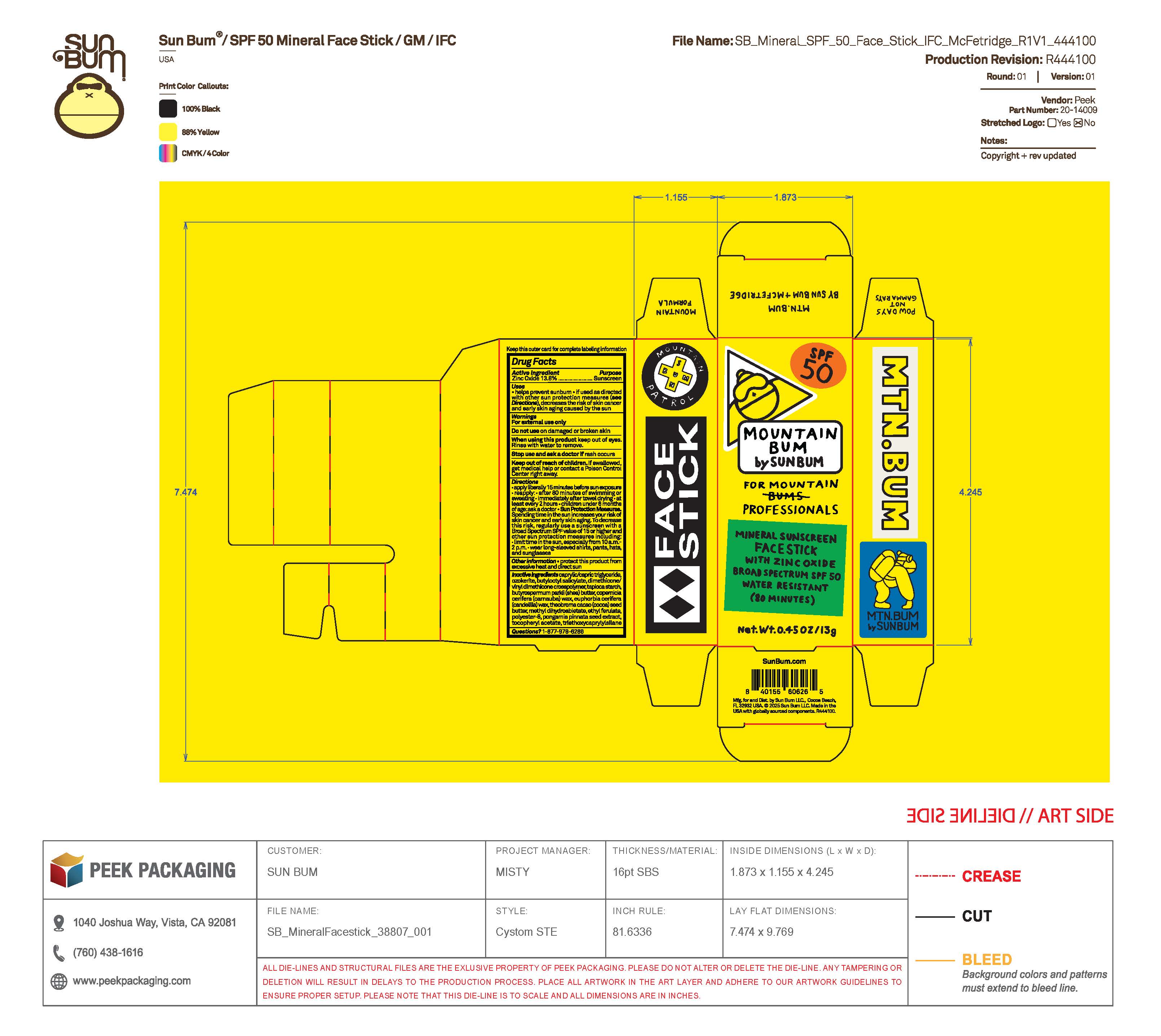 DRUG LABEL: Mtn. Bum by Sun Bum and Mcfetridge Mineral Sunscreen Face Stick SPF 50
NDC: 69039-835 | Form: STICK
Manufacturer: Sun Bum, LLC
Category: otc | Type: HUMAN OTC DRUG LABEL
Date: 20250923

ACTIVE INGREDIENTS: ZINC OXIDE 138 mg/1 g
INACTIVE INGREDIENTS: EUPHORBIA CERIFERA (CANDELILLA) WAX; TRIETHOXYCAPRYLYLSILANE; BUTYROSPERMUM PARKII (SHEA) BUTTER; CERESIN; METHYL DIHYDROABIETATE; DIMETHICONE/VINYL DIMETHICONE CROSSPOLYMER (SOFT PARTICLE); CAPRYLIC/CAPRIC TRIGLYCERIDE; TAPIOCA STARCH; COPERNICIA CERIFERA (CARNAUBA) WAX; THEOBROMA CACAO (COCOA) SEED BUTTER; BUTYLOCTYL SALICYLATE; ETHYL FERULATE; POLYESTER-8 (1400 MW, CYANODIPHENYLPROPENOYL CAPPED); .ALPHA.-TOCOPHEROL ACETATE; PONGAMIA PINNATA SEED

Mtn. Bum by Sun Bum and Mcfetridge Mineral Sunscreen Face Stick SPF 50

Active Ingredients

Zinc Oxide 13.8%

Purpose

Sunscreen

Uses

• helps prevent sunburn • if used as directed with other sun protection measures, (see Directions) decreases the risk of skin cancer and early skin aging caused by the sun

Warnings

For external use only.

Do not use on damaged or broken skin

When using this product keep out of eyes. Rinse with water to remove.

Stop use and ask a doctor if rash occurs

Keep out of reach of children. If swallowed, get medical help or contact a Poison Control Center right away.

Warnings

Keep Out Of Reach Of Children

Directions

• apply liberally 15 minutes before sun exposure

• reapply: • after 80 minutes of swimming or sweating • immediately after towel drying • at least every 2 hours

• children under 6 months of age: ask a doctor

• Sun Protection Measures. Spending time in the sun increases your risk of skin cancer and early skin aging. To decrease this risk, regularly use a sunscreen with a Broad Spectrum SPF value of 15 or higher and other sun protection measures including:

• limit time in the sun, especially from 10 a.m.- 2 p.m.

• wear long-sleeved shirts, pants, hats and sunglasses

Directions

• apply liberally 15 minutes before sun exposure

Other Information

protect this product from excessive heat and direct sun

Inactive Ingredients

CAPRYLIC/CAPRIC TRIGLYCERIDE, OZOKERITE, BUTYLOCTYL SALICYLATE, DIMETHICONE/VINYL DIMETHICONE CROSSPOLYMER, TAPIOCA STARCH, BUTYROSPERMUM PARKII (SHEA) BUTTER, COPERNICIA CERIFERA (CARNAUBA) WAX, EUPHORBIA CERIFERA (CANDELILLA) WAX, THEOBROMA CACAO (COCOA) SEED BUTTER, METHYL DIHYDROABIETATE, ETHYL FERULATE, POLYESTER-8, PONGAMIA PINNATA SEED EXTRACT, TOCOPHEROL ACETATE, TRIETHOXYCAPRYLYLSILANE

Questions?

1-877-978-6286